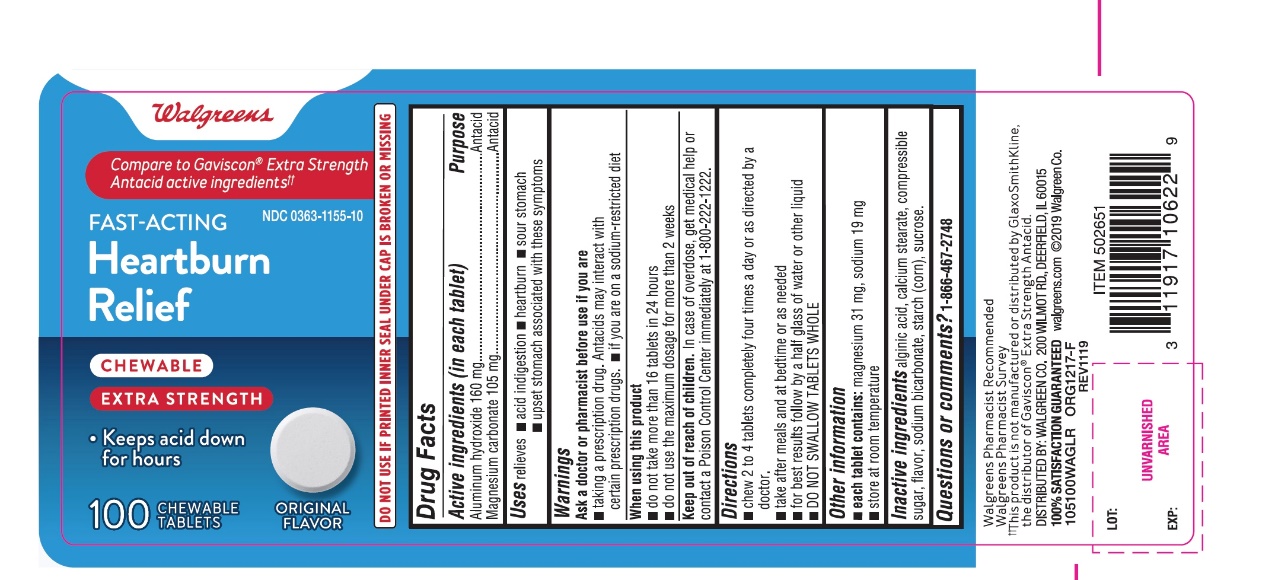 DRUG LABEL: FAST ACTING Heartburn Relief
NDC: 0363-1155 | Form: TABLET, CHEWABLE
Manufacturer: WALGREEN CO.
Category: otc | Type: HUMAN OTC DRUG LABEL
Date: 20251125

ACTIVE INGREDIENTS: ALUMINUM HYDROXIDE 160 mg/1 1; MAGNESIUM CARBONATE 105 mg/1 1
INACTIVE INGREDIENTS: ALGINIC ACID; CALCIUM STEARATE; CORN SYRUP; SODIUM BICARBONATE; STARCH, CORN; SUCROSE

FAST ACTING Heartburn Relief Chewable Extra Strength Original Flavor 100 Chewable Tablets

Active ingredients (in each tablet)

Aluminum hydroxide 160 mg

Magnesium carbonate 105 mg

Purpose

Antacid

Antacid

Uses

relieves

- acid indigestion
- heartburn
- sour stomach
- upset stomach associated with these symptoms

Warnings

Ask a doctor or pharmacist before use if you are

- taking a prescription drug. Antacids may interact with certain prescription drugs
- If you are on a sodium-restricted diet

When using this product

- do not take more than 16 tablets in 24 hours
- do not use the maximum dosage for more than 2 weeks

Keep out of reach of children.

In case of overdose, get medical help or contact a Poison Control Center immediately at 1-800-222-1222

Directions

- chew 2 to 4 tablets completely four times a day or as directed by a doctor.
- take after meals and at bedtime or as needed
- for best results follow by a half glass of water or other liquid
- DO NOT SWALLOW TABLETS WHOLE

Other information

- each tablet contains: magnesium 31 mg, sodium 19 mg,
- store at room temperature

Inactive ingredients

alginic acid, calcium stearate, compressible sugar, flavor, sodium bicarbonate, starch (corn), sucrose.

Questions or comments?

1-866-467-2748

Principal Display Panel

Walgreens

Compare to Gaviscon® Extra Strength Antacid active ingredients††

NDC 0363-1155-10

FAST-ACTING

Heartburn

Relief

CHEWABLE

EXTRA STRENGTH

- Keeps acid down for hours

ORIGINAL FLAVOR

100 CHEWABLE TABLETS

WALGREENS PHARMACIST RECOMMENDED

Walgreens Pharmacist Survey

††This product is not manufactured or distributed by GlaxoSmithKline, the distributor of Gaviscon® Extra Strength.

DISTRIBUTED BY: WALGREEN CO.

200 WILMOT RD. DEERFIELD, IL 60015

100% SATISFACTION GUARANTEED

Walgreens.com ©2019 Walgreen Co

105100WAGLR

ORG1217-F

REV1119